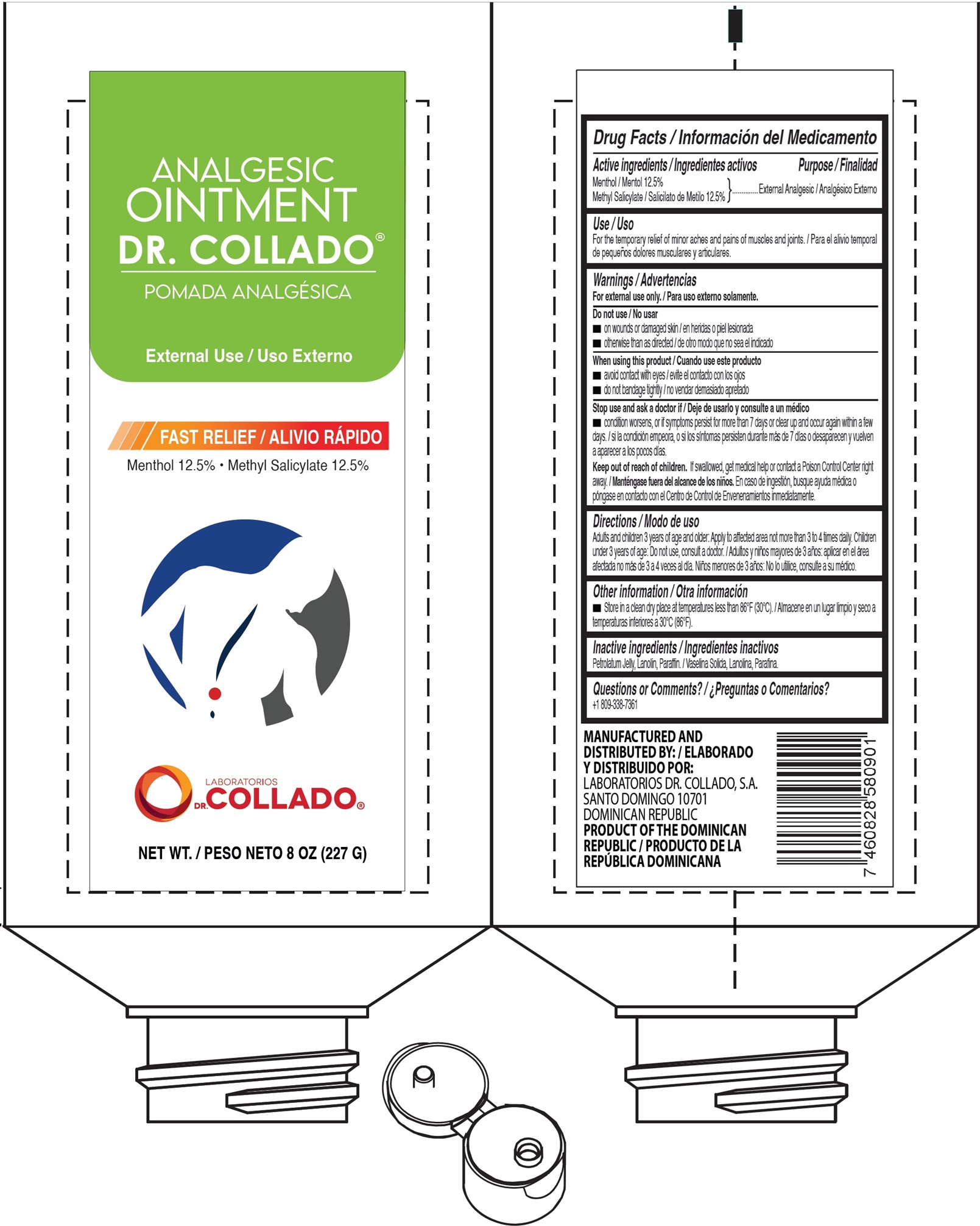 DRUG LABEL: Analgesic Dr. Collado
NDC: 42333-001 | Form: OINTMENT
Manufacturer: Laboratorios Dr. Collado, S.A
Category: otc | Type: HUMAN OTC DRUG LABEL
Date: 20260129

ACTIVE INGREDIENTS: MENTHOL 125 mg/1 g; METHYL SALICYLATE 125 mg/1 g
INACTIVE INGREDIENTS: PETROLATUM; LANOLIN; PARAFFIN

Analgesic Ointment Dr. Collado Menthol

Active ingredients

Menthol 12.5%

Methyl Salicylate 12.5%

Purpose

External Analgesic

Use

For the temporary relief of minor aches and pains of muscles and joints.

Warnings

For external use only.

Do not use

- on wounds or damaged skin
- otherwise than as directed

When using this product

- avoid contact with eyes
- do not bandage tightly

Stop use and ask a doctor if

- condition worsens, or if symptoms persist for more than 7 days or clear up and occur again within a few days.

Keep out of reach of children.

If swallowed, get medical help or contact a Poison Control Center right away.

Directions

Adults and children 3 years of age and older: Apply to affected area not more than 3 to 4 times daily. Children under 3 years of age: Do not use, consult a doctor.

Other information

- Store in a clean dry place at temperatures less than 86°F (30°C).

Inactive ingredients

Petrolatum Jelly, Lanolin, Paraffin.

Questions or Comments?

+1 809-338-7361